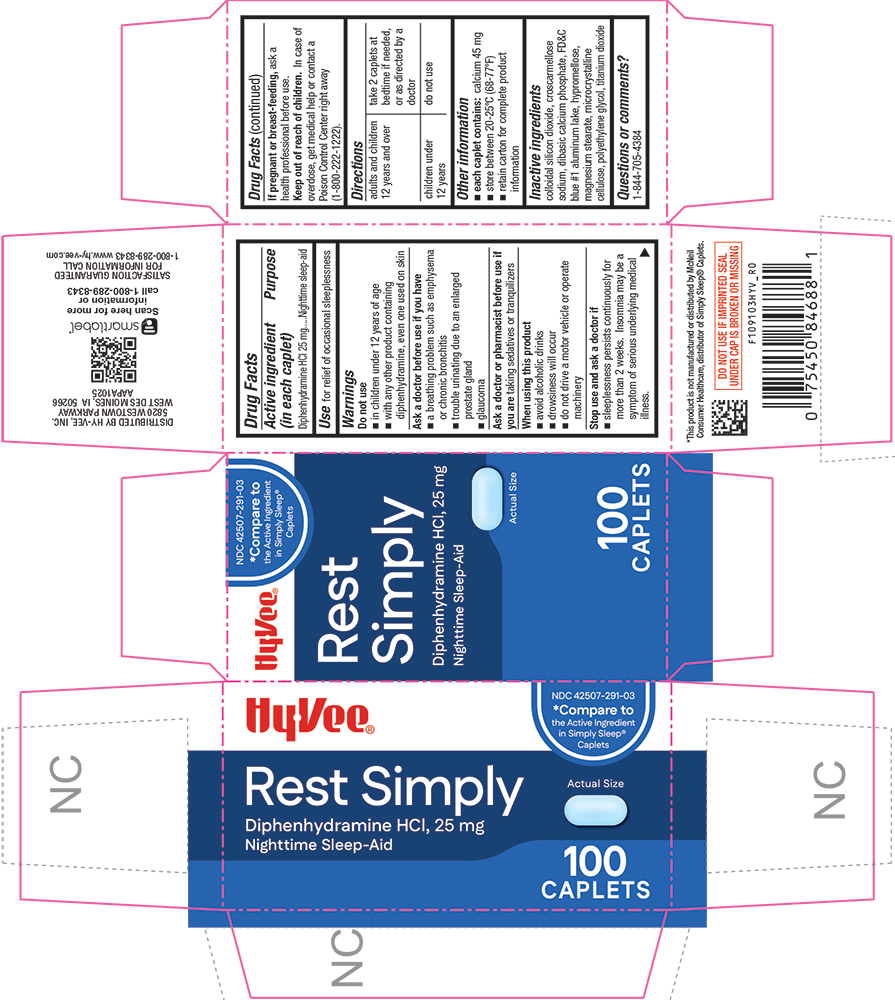 DRUG LABEL: Rest Simply
NDC: 42507-291 | Form: TABLET, COATED
Manufacturer: HYVEE INC
Category: otc | Type: HUMAN OTC DRUG LABEL
Date: 20260113

ACTIVE INGREDIENTS: DIPHENHYDRAMINE HYDROCHLORIDE 25 mg/1 1
INACTIVE INGREDIENTS: SILICON DIOXIDE; CROSCARMELLOSE SODIUM; CALCIUM PHOSPHATE, DIBASIC, ANHYDROUS; FD&C BLUE NO. 1; HYPROMELLOSES; MAGNESIUM STEARATE; CELLULOSE, MICROCRYSTALLINE; POLYETHYLENE GLYCOL, UNSPECIFIED; TITANIUM DIOXIDE; ALUMINUM OXIDE

1091-HYV-2026-0113

Drug Facts

Active ingredient (in each caplet)

Diphenhydramine HCl 25 mg

Purpose

Nighttime sleep-aid

Use

for relief of occasional sleeplessness

Warnings

Do not use

- in children under 12 years of age
- with any other product containing diphenhydramine, even one used on skin

Ask a doctor before use if you have

- a breathing problem such as emphysema or chronic bronchitis
- trouble urinating due to an enlarged prostate gland
- glaucoma

Ask a doctor or pharmacist before use if you aretaking sedatives or tranquilizers

When using this product

- avoid alcoholic drinks
- drowsiness will occur
- do not drive a motor vehicle or operate machinery

Stop use and ask a doctor if

- sleeplessness persists continously for more than 2 weeks. Insomnia may be a symptom of serious underlying medical illness.

PREGNANCY OR BREAST FEEDING

If pregnant or breast-feeding,ask a health professional before use.

Keep out of reach of children.In case of overdose, get medical help or contact a Poison Control Center right away (1-800-222-1222).

Directions

adults and children 12 years of age and over | take 2 caplets at bedtime if needed, or as directed by a doctor
children under 12 years of age | do not use

Other information

- each caplet contains:calcium 45 mg
- store at room temperature 20-25°C (68-77°F)
- retain carton for complete product information

Inactive ingredients

colloidal silicon dioxide, croscarmellose sodium, dibasic calcium phosphate, FD&C blue #1aluminum lake, hypromellose, magnesium stearate, microcrystalline cellulose, polyethylene glycol, titanium dioxide

Questions or comments?

1-844-705-4384

PRINCIPAL DISPLAY PANEL

HyVee®

NDC 42507-291-03

*Compare to the Active Ingredient in Simply Sleep® Caplets

Rest Simply

Diphenhydramine HCl, 25 mg

Nighttime Sleep-Aid

Actual Size

100 CAPLETS